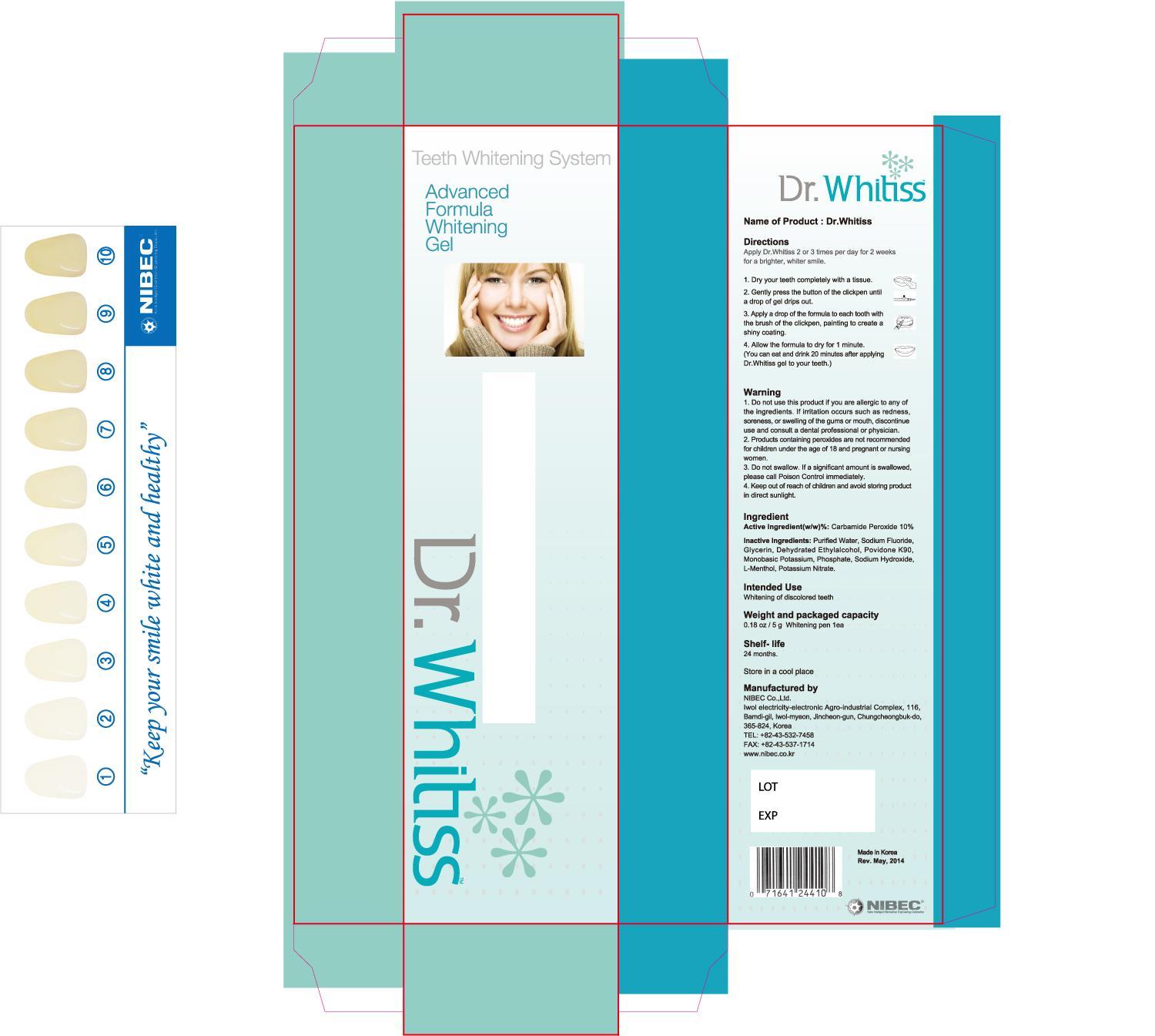 DRUG LABEL: Dr. Whitiss (8.3%)
NDC: 47649-9001 | Form: GEL, DENTIFRICE
Manufacturer: Nibec Co., Ltd
Category: otc | Type: HUMAN OTC DRUG LABEL
Date: 20171127

ACTIVE INGREDIENTS: CARBAMIDE PEROXIDE 0.083 g/1 g
INACTIVE INGREDIENTS: POVIDONE K90; GLYCERIN; WATER; POTASSIUM NITRATE

Drug Facts

ACTIVE INGREDIENT

carbamide peroxide

INACTIVE INGREDIENT

polyvinyl pyrrolidone (k=90), glycerin, anhydrous ethyl alcohol, distilled water, potassium dihydrogen phosphate, sodium hydroxide, lemon oil, orange oil, xylitol, l-menthol, potassium nitrate, propolis ext

PURPOSE

whitening of discolored vital teeth

keep out of reach of the children

INDICATIONS AND USAGE

apply 2 or 3 times per day for 2 weeks for a brighter, whiter smile

WARNINGS

1) do not use on patient with sensitive to carbamide peroxide
2) do not use on patient with oral infection
3) no to be used by pregnant or lactating women or children under 18 years old
4) to be used under the supervision of a dentist
5) do not swallow this medication

DOSAGE AND ADMINISTRATION

for dental use only